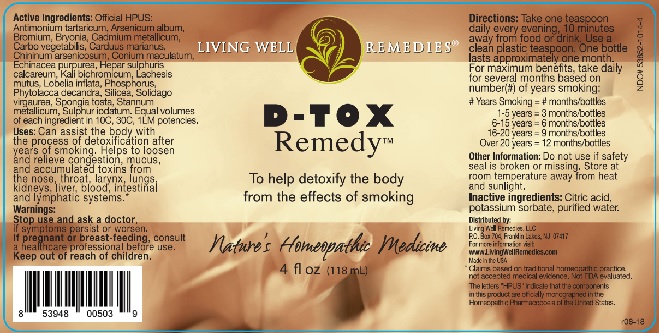 DRUG LABEL: D-TOX Remedy
NDC: 53852-1014 | Form: LIQUID
Manufacturer: Living Well Remedies, LLC
Category: homeopathic | Type: HUMAN OTC DRUG LABEL
Date: 20181005

ACTIVE INGREDIENTS: ANTIMONY POTASSIUM TARTRATE 10 [hp_C]/118 mL; BROMINE 10 [hp_C]/118 mL; BRYONIA ALBA ROOT 10 [hp_C]/118 mL; ACTIVATED CHARCOAL 10 [hp_C]/118 mL; MILK THISTLE 10 [hp_C]/118 mL; ECHINACEA PURPUREA 10 [hp_C]/118 mL; CALCIUM SULFIDE 10 [hp_C]/118 mL; POTASSIUM DICHROMATE 10 [hp_C]/118 mL; LOBELIA INFLATA 10 [hp_C]/118 mL; PHOSPHORUS 10 [hp_C]/118 mL; PHYTOLACCA AMERICANA ROOT 10 [hp_C]/118 mL; SILICON DIOXIDE 10 [hp_C]/118 mL; SOLIDAGO VIRGAUREA FLOWERING TOP 10 [hp_C]/118 mL; SPONGIA OFFICINALIS SKELETON, ROASTED 10 [hp_C]/118 mL; SULFUR IODIDE 10 [hp_C]/118 mL; ARSENIC TRIOXIDE 10 [hp_C]/118 mL; CADMIUM 10 [hp_C]/118 mL; CONIUM MACULATUM FLOWERING TOP 10 [hp_C]/118 mL; QUININE ARSENATE 10 [hp_C]/118 mL; LACHESIS MUTA VENOM 10 [hp_C]/118 mL
INACTIVE INGREDIENTS: CITRIC ACID MONOHYDRATE; POTASSIUM SORBATE; WATER

D-TOX Remedy™

ACTIVE INGREDIENT

Active Ingredients: Official HPUS: Antimonium tartaricum, Arsenicum album, Bromium, Bryonia, Cadmium metallicum, Carbo vegetabilis, Carduus marianus, Chininum arsenicosum, Conium maculatum, Echinacea purpurea, Hepar sulphuris calcareum, Kali bichromicum, Lachesis mutus, Lobelia inflata, Phosphorus, Phytolacca decandra, Silicea, Solidago virgaurea, Spongia tosta, Stannum metallicum, Sulphur iodatum. Equal volumes of each ingredient in 10C, 30C, 1LM potencies.

*Claims based on traditional homeopathic practice, not accepted medical evidene. Not FDA evaluated.

The letters "HPUS" indicate that the compnents in this product are offically monographed in the Homeopathic Pharmecopeia of the United States.

INDICATIONS AND USAGE

Uses: Can assist the body with the process of detoxification after years of smoking. Helps to loosen and relieve congestion, mucus, and accumulated toxins from the nose, throat, larynx, lungs, kidneys, liver, blood, intestinal and lymphatic systems.*

WARNINGS

Warnings: Stop use and ask a doctor, if symptoms persist or worsen. If pregnant or breast-feeding, consult a health care professional before use.

Keep out of reach of children.

DOSAGE AND ADMINISTRATION

Directions: Take one teaspoon daily every evening, 10 minutes away from food or drink. Use a clean plastic teaspoon. One bottle lasts approximately one month. For maximum benefits, take daily for several months based on number(#) of years smoking:

# Years Smoking = # months/bottles

1-5 years = 3 months/bottles

6-15 years = 6 months/bottles

16-20 years = 9 months/bottles

over 20 years =12 months/bottles

Other Information: Do not use if safety seal is broken or missing. Store at room temperature away from heat and sunlight.

Inactive ingredients: Citric acid, potassium sorbate, purified water.

QUESTIONS

Distributed by:

Living Well Remedies, LLC

P.O. Box 704 Franklin Lakes, NJ 07417

www.LivingWellRemedies.com

Made in the USA

PACKAGE LABEL

LIVING WELL REMEDIES®

D-TOX

Remedy™

To help detoxify the body

from the effects of smoking

Nature's Homeopathic Medicine

4 fl oz (118mL)

PURPOSE

To help detoxify the body

from the effects of smoking